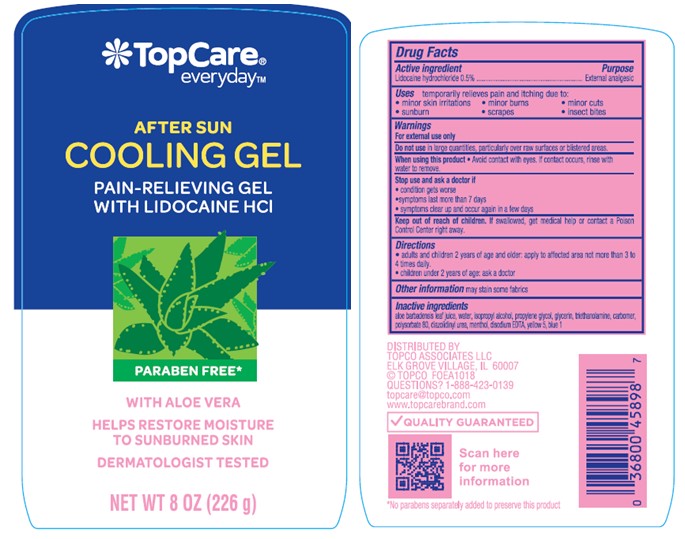 DRUG LABEL: TopCare Everyday After Sun Cooling
NDC: 36800-953 | Form: GEL
Manufacturer: TOPCO ASSOCIATES LLC
Category: otc | Type: HUMAN OTC DRUG LABEL
Date: 20241015

ACTIVE INGREDIENTS: LIDOCAINE HYDROCHLORIDE 5 mg/1 g
INACTIVE INGREDIENTS: ALOE VERA LEAF; TROLAMINE; FD&C BLUE NO. 1; POLYSORBATE 80; DIAZOLIDINYL UREA; WATER; MENTHOL; FD&C YELLOW NO. 5; CARBOMER INTERPOLYMER TYPE A (55000 CPS); PROPYLENE GLYCOL; EDETATE DISODIUM; ISOPROPYL ALCOHOL; GLYCERIN

TopCare Everyday After Sun Cooling Gel

Active Ingredient

Lidocaine hydrochloride 0.5%

Purpose

External Analgesic

Uses

temporarily relieves pain and itching due to:

- minor skin irritations
- sunburn
- minor burns
- scrapes
- minor cuts
- insect bites

Warnings

- For External Use Only

Do not use

in large quantities, particularly over raw surfaces or blistered areas.

When using this product

- avoid contact with eyes. If contact occurs, rinse with water to remove.

Stop use and ask a doctor if

- condition gets worse
- symptoms last more than 7 days
- symptoms clear up and occur again in a few days

Keep out of reach of children.

If swallowed, get medical help or contact a Poison Control Center right away.

Directions

- adults and children 2 years of age and older: apply to affected area not more than 3 to 4 times daily.
- children under 2 years of age: ask a doctor

Inactive Ingredients

aloe barbadensis leaf juice, water, isopropyl alcohol, propylene glycol, glycerin, triethanolamine, carbomer, polysorbate 80, diazolidinyl urea, menthol, disodium EDTA, yellow 5, blue 1

Label

TopCare Everyday After Sun Cooling Gel

8 OZ (226 g)

NDC 36800-953-80